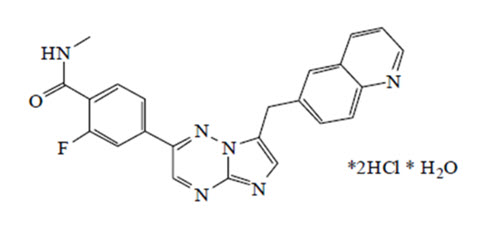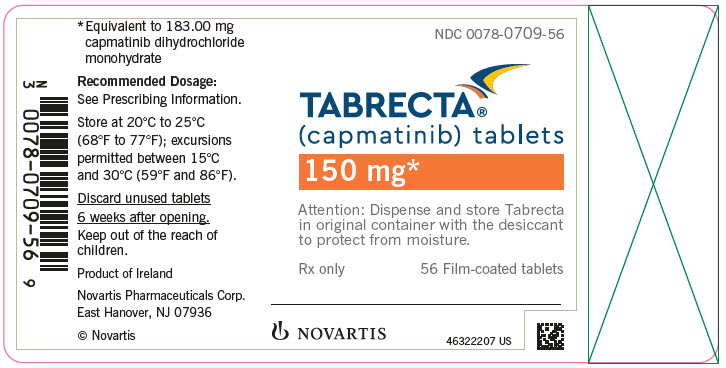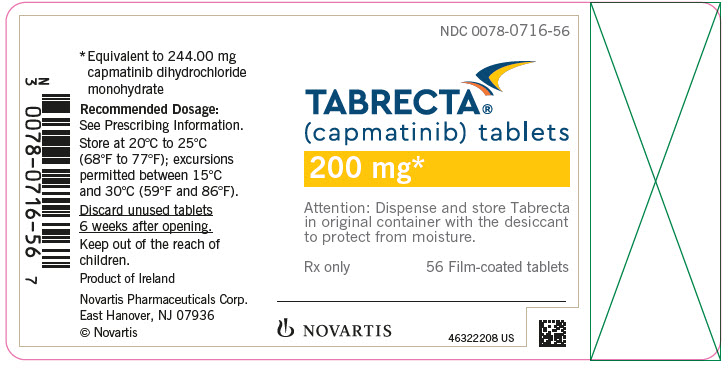 DRUG LABEL: TABRECTA
NDC: 0078-0709 | Form: TABLET, FILM COATED
Manufacturer: Novartis Pharmaceuticals Corporation
Category: prescription | Type: HUMAN PRESCRIPTION DRUG LABEL
Date: 20251215

ACTIVE INGREDIENTS: CAPMATINIB HYDROCHLORIDE 150 mg/1 1
INACTIVE INGREDIENTS: SILICON DIOXIDE; CROSPOVIDONE; MAGNESIUM STEARATE; MANNITOL; CELLULOSE, MICROCRYSTALLINE; POVIDONE; SODIUM LAURYL SULFATE; FERRIC OXIDE RED; FERRIC OXIDE YELLOW; FERROSOFERRIC OXIDE; HYPROMELLOSES; POLYETHYLENE GLYCOL 400; TALC; TITANIUM DIOXIDE

HIGHLIGHTS OF PRESCRIBING INFORMATION

These highlights do not include all the information needed to use TABRECTA safely and effectively. See full prescribing information for TABRECTA.
TABRECTA® (capmatinib) tablets, for oral use
Initial U.S. Approval: 2020

1 INDICATIONS AND USAGE

TABRECTA is a kinase inhibitor indicated for the treatment of adult patients with metastatic non-small cell lung cancer (NSCLC) whose tumors have a mutation that leads to mesenchymal-epithelial transition (MET) exon 14 skipping as detected by an FDA-approved test.

2 DOSAGE AND ADMINISTRATION

- Select patients for treatment with TABRECTA based on presence of a mutation that leads to MET exon 14 skipping. (2.1)
- Recommended Dosage: 400 mg orally twice daily with or without food. (2.2)

3 DOSAGE FORMS AND STRENGTHS

Tablets: 150 mg and 200 mg

4 CONTRAINDICATIONS

None.

5 WARNINGS AND PRECAUTIONS

- Interstitial Lung Disease (ILD)/Pneumonitis: Monitor for new or worsening pulmonary symptoms indicative of ILD/pneumonitis. Permanently discontinue TABRECTA in patients with ILD/pneumonitis. (2.3, 5.1)
- Hepatotoxicity: Monitor liver function tests. Withhold, dose reduce, or permanently discontinue TABRECTA based on severity. (2.3, 5.2)
- Pancreatic Toxicity: Monitor amylase and lipase levels. Withhold, dose reduce, or permanently discontinue TABRECTA based on severity. (2.3, 5.3)
- Hypersensitivity Reactions: Withhold or permanently discontinue TABRECTA based on severity. (2.3, 5.4)
- Risk of Photosensitivity: May cause photosensitivity reactions. Advise patients to limit direct ultraviolet exposure. (5.5)
- Embryo-Fetal Toxicity: Can cause fetal harm. Advise patients of the potential risk to a fetus and to use effective contraception. (5.6, 8.1, 8.3)

6 ADVERSE REACTIONS

The most common adverse reactions (≥ 20%) are edema, nausea, musculoskeletal pain, fatigue, vomiting, dyspnea, cough, and decreased appetite. (6)

To report SUSPECTED ADVERSE REACTIONS, contact Novartis Pharmaceuticals Corporation at 1-888-669-6682 or FDA at 1-800-FDA-1088 or www.fda.gov/medwatch.

7 DRUG INTERACTIONS

Strong and Moderate CYP3A Inducers: Avoid concomitant use. (7.1)

8 USE IN SPECIFIC POPULATIONS

Lactation: Advise not to breastfeed. (8.2)

FULL PRESCRIBING INFORMATION

1 INDICATIONS AND USAGE

TABRECTA is indicated for the treatment of adult patients with metastatic non-small cell lung cancer (NSCLC) whose tumors have a mutation that leads to mesenchymal-epithelial transition (MET) exon 14 skipping as detected by an FDA-approved test.

2 DOSAGE AND ADMINISTRATION

2.1 Patient Selection

Select patients for treatment with TABRECTA based on the presence of a mutation that leads to MET exon 14 skipping in tumor or plasma specimens [see Clinical Studies (14)]. If a mutation that leads to MET exon 14 skipping is not detected in a plasma specimen, test tumor tissue if feasible. Information on FDA-approved tests is available at: http://www.fda.gov/CompanionDiagnostics.

2.2 Recommended Dosage

The recommended dosage of TABRECTA is 400 mg orally twice daily with or without food.

Swallow TABRECTA tablets whole. Do not break, crush or chew the tablets.

If a patient misses or vomits a dose, instruct the patient not to make up the dose, but to take the next dose at its scheduled time.

2.3 Dosage Modifications for Adverse Reactions

The recommended dose reductions for the management of adverse reactions are listed in Table 1.

Table 1: Recommended TABRECTA Dose Reductions for Adverse Reactions
Dose reduction | Dose and schedule
First | 300 mg orally twice daily
Second | 200 mg orally twice daily

Permanently discontinue TABRECTA in patients who are unable to tolerate 200 mg orally twice daily.

The recommended dosage modifications of TABRECTA for adverse reactions are provided in Table 2.

Table 2: Recommended TABRECTA Dosage Modifications for Adverse Reactions
Adverse reaction | Severity | Dosage modification
Interstitial Lung Disease (ILD)/Pneumonitis [see Warnings and Precautions (5.1)] | Any grade | Permanently discontinue TABRECTA.
Increased ALT and/or AST without increased total bilirubin [see Warnings and Precautions (5.2)] | Grade 3 | Withhold TABRECTA until recovery to baseline ALT/AST. If recovered to baseline within 7 days, then resume TABRECTA at the same dose; otherwise resume TABRECTA at a reduced dose.
Increased ALT and/or AST without increased total bilirubin [see Warnings and Precautions (5.2)] | Grade 4 | Permanently discontinue TABRECTA.
Increased ALT and/or AST with increased total bilirubin in the absence of cholestasis or hemolysis [see Warnings and Precautions (5.2)] | ALT and/or AST greater than 3 times ULN with total bilirubin greater than 2 times ULN | Permanently discontinue TABRECTA.
Increased total bilirubin without concurrent increased ALT and/or AST [see Warnings and Precautions (5.2)] | Grade 2 | Withhold TABRECTA until recovery to baseline bilirubin. If recovered to baseline within 7 days, then resume TABRECTA at the same dose; otherwise resume TABRECTA at a reduced dose.
Increased total bilirubin without concurrent increased ALT and/or AST [see Warnings and Precautions (5.2)] | Grade 3 | Withhold TABRECTA until recovery to baseline bilirubin. If recovered to baseline within 7 days, then resume TABRECTA at a reduced dose; otherwise permanently discontinue TABRECTA.
Increased total bilirubin without concurrent increased ALT and/or AST [see Warnings and Precautions (5.2)] | Grade 4 | Permanently discontinue TABRECTA.
Increased lipase or amylase [see Warnings and Precautions (5.3)] | Grade 3 | Withhold TABRECTA until ≤ Grade 2 or baseline. If recovered to baseline or ≤ Grade 2 within 14 days, resume TABRECTA at a reduced dose; otherwise permanently discontinue TABRECTA.
 | Grade 4 | Permanently discontinue TABRECTA.
Pancreatitis [see Warnings and Precautions (5.3)] | Grade 3 or Grade 4 | Permanently discontinue TABRECTA.
Hypersensitivity [see Warnings and Precautions (5.4)] | All Grades | If hypersensitivity is suspected based on clinical judgment, withhold TABRECTA until resolution of the event. Permanently discontinue TABRECTA in patients who develop serious hypersensitivity reactions.
Other adverse reactions [see Adverse Reactions (6.1)] | Grade 2 | Maintain dose level. If intolerable, consider withholding TABRECTA until resolved, then resume TABRECTA at a reduced dose.
Other adverse reactions [see Adverse Reactions (6.1)] | Grade 3 | Withhold TABRECTA until resolved, then resume TABRECTA at a reduced dose.
Other adverse reactions [see Adverse Reactions (6.1)] | Grade 4 | Permanently discontinue TABRECTA.
Abbreviations: ALT, alanine aminotransferase; AST, aspartate aminotransferase; ILD, interstitial lung disease; ULN, upper limit of normal.
Grading according to Common Terminology Criteria for Adverse Events (CTCAE) version 5.0.

3 DOSAGE FORMS AND STRENGTHS

Tablets:

- 150 mg: pale orange brown, ovaloid, curved film-coated with beveled edges, unscored, debossed with ‘DU’ on one side and ‘NVR’ on the other side
- 200 mg: yellow, ovaloid, curved film-coated with beveled edges, unscored, debossed with ‘LO’ on one side and ‘NVR’ on the other side

4 CONTRAINDICATIONS

None.

5 WARNINGS AND PRECAUTIONS

5.1 Interstitial Lung Disease (ILD)/Pneumonitis

ILD/pneumonitis, which can be fatal, occurred in patients treated with TABRECTA [see Adverse Reactions (6.1)]. ILD/pneumonitis occurred in 4.8% of patients treated with TABRECTA in GEOMETRY mono-1, with 1.9% of patients experiencing Grade 3 ILD/pneumonitis and one patient experiencing death (0.3%). Nine patients (2.4%) discontinued TABRECTA due to ILD/pneumonitis. The median time-to-onset of Grade 3 or higher ILD/pneumonitis was 1.8 months (range: 0.2 months to 1.7 years).

Monitor for new or worsening pulmonary symptoms indicative of ILD/pneumonitis (e.g., dyspnea, cough, fever). Immediately withhold TABRECTA in patients with suspected ILD/pneumonitis and permanently discontinue if no other potential causes of ILD/pneumonitis are identified [see Dosage and Administration (2.3)].

5.2 Hepatotoxicity

Hepatotoxicity occurred in patients treated with TABRECTA [see Adverse Reactions (6.1)]. Increased alanine aminotransferase (ALT)/aspartate aminotransferase (AST) occurred in 15% of patients treated with TABRECTA in GEOMETRY mono-1. Grade 3 or 4 increased ALT/AST occurred in 7% of patients. Three patients (0.8%) discontinued TABRECTA due to increased ALT/AST. The median time-to-onset of Grade 3 or higher increased ALT/AST was 1.8 months (range: 0.5 to 46.4 months).

Monitor liver function tests (including ALT, AST, and total bilirubin) prior to the start of TABRECTA, every 2 weeks during the first 3 months of treatment, then once a month or as clinically indicated, with more frequent testing in patients who develop increased transaminases or bilirubin. Based on the severity of the adverse reaction, withhold, dose reduce, or permanently discontinue TABRECTA [see Dosage and Administration (2.3)].

5.3 Pancreatic Toxicity

Elevations in amylase and lipase levels occurred in patients treated with TABRECTA [see Adverse Reactions (6.1)]. Increased amylase/lipase occurred in 14% of patients treated with TABRECTA in GEOMETRY mono-1. Grade 3 and 4 increased amylase/lipase occurred in 7% and 1.9% of patients, respectively. Three patients (0.8%) discontinued TABRECTA due to increased amylase/lipase. The median time-to-onset of Grade 3 or higher increased amylase/lipase was 2 months (range: 0.03 to 31.1 months). Pancreatitis (Grade 3) occurred in one patient (0.3%); TABRECTA was permanently discontinued for this event.

Monitor amylase and lipase at baseline and regularly during treatment with TABRECTA. Based on the severity of the adverse reaction, temporarily withhold, dose reduce, or permanently discontinue TABRECTA [see Dosage and Administration (2.3)].

5.4 Hypersensitivity Reactions

Serious hypersensitivity reactions occurred in patients treated with TABRECTA in clinical trials other than GEOMETRY mono-1 [see Adverse Reactions (6.1)]. Signs and symptoms of hypersensitivity included pyrexia, chills, pruritus, rash, decreased blood pressure, nausea and vomiting. Based on the severity of the adverse reaction, temporarily withhold or permanently discontinue TABRECTA [see Dosage and Administration (2.3)].

5.5 Risk of Photosensitivity

Based on findings from animal studies, there is a potential risk of photosensitivity reactions with TABRECTA [see Nonclinical Toxicology (13.2)]. In GEOMETRY mono-1, it was recommended that patients use precautionary measures against ultraviolet exposure such as use of sunscreen or protective clothing during treatment with TABRECTA. Advise patients to limit direct ultraviolet exposure during treatment with TABRECTA.

5.6 Embryo-Fetal Toxicity

Based on findings from animal studies and its mechanism of action, TABRECTA can cause fetal harm when administered to a pregnant woman. Oral administration of capmatinib to pregnant rats and rabbits during the period of organogenesis resulted in malformations at exposures less than the human exposure based on area under the curve (AUC) at the 400 mg twice daily clinical dose. Advise pregnant women of the potential risk to a fetus. Advise females of reproductive potential to use effective contraception during treatment with TABRECTA and for 1 week after the last dose. Advise males with female partners of reproductive potential to use effective contraception during treatment with TABRECTA and for 1 week after the last dose [see Use in Specific Populations (8.1, 8.3)].

6 ADVERSE REACTIONS

The following clinically significant adverse reactions are described elsewhere in the labeling:

- ILD/Pneumonitis [see Warnings and Precautions (5.1)]
- Hepatotoxicity [see Warnings and Precautions (5.2)]
- Pancreatic Toxicity [see Warnings and Precautions (5.3)]
- Hypersensitivity reactions [see Warnings and Precautions (5.4)]

6.1 Clinical Trials Experience

Because clinical trials are conducted under widely varying conditions, adverse reaction rates observed in the clinical trials of a drug cannot be directly compared to rates in the clinical trials of another drug and may not reflect the rates observed in practice.

Metastatic Non-Small Cell Lung Cancer

The safety of TABRECTA was evaluated in GEOMETRY mono-1 [see Clinical Studies (14)]. Patients received TABRECTA 400 mg orally twice daily until disease progression or unacceptable toxicity (N = 373). Among patients who received TABRECTA, 37% were exposed for at least 6 months and 22% were exposed for at least one year.

Serious adverse reactions occurred in 53% of patients who received TABRECTA. Serious adverse reactions in ≥ 2% of patients included dyspnea (7%), pneumonia (7%), pleural effusion (4.3%), musculoskeletal pain (3.8%), general physical health deterioration (2.9%), ILD/pneumonitis (2.7%), edema (2.4%), and vomiting (2.4%). Fatal adverse reactions occurred in 0.5% of patients who received TABRECTA, including pneumonitis (0.3%) and death, not otherwise specified (0.3%).

Permanent discontinuation of TABRECTA due to an adverse reaction occurred in 17% of patients. The most frequent adverse reactions (≥ 1%) leading to permanent discontinuation of TABRECTA were ILD/pneumonitis (2.4%), edema (2.4%), fatigue (1.3%), and pneumonia (1.1%).

Dose interruptions due to an adverse reaction occurred in 57% of patients who received TABRECTA. Adverse reactions requiring dosage interruption in > 2% of patients who received TABRECTA included edema, increased blood creatinine, nausea, increased lipase, vomiting, increased ALT, dyspnea, pneumonia, fatigue, increased amylase, increased AST, musculoskeletal pain, abdominal pain, and increased blood bilirubin.

Dose reductions due to an adverse reaction occurred in 26% of patients who received TABRECTA. Adverse reactions requiring dosage reductions in > 2% of patients who received TABRECTA included edema, increased ALT and increased blood creatinine.

The most common adverse reactions (≥ 20%) in patients who received TABRECTA were edema, nausea, musculoskeletal pain, fatigue, vomiting, dyspnea, cough, and decreased appetite.

Table 3 summarizes the adverse reactions in GEOMETRY mono-1.

Table 3: Adverse Reactions (≥ 10%) in Patients Who Received TABRECTA in GEOMETRY mono-1
Adverse reactions | TABRECTA (N = 373)
 | Grades 1 to 4 (%) | Grades 3 to 4 (%)
General disorders and administration-site conditions
Edemaa | 59 | 13
Musculoskeletal painb | 40 | 4.3
Fatiguec | 34 | 8
Pyrexiad | 14 | 0.8
Weight decreased | 11 | 0.5
Gastrointestinal disorders
Nausea | 46 | 2.4
Vomiting | 28 | 2.4
Constipation | 19 | 0.8
Diarrhea | 19 | 0.5
Respiratory, thoracic, and mediastinal disorders
Dyspnea | 25 | 7
Coughe | 21 | 0.5
Pneumoniaf | 13 | 6
Metabolism and nutrition disorders
Decreased appetite | 21 | 1.1
Skin and subcutaneous tissue disorders
Rashg | 13 | 0.5
Nervous system disorders
Dizzinessh | 13 | 0.5
aEdema includes edema peripheral, generalized edema, face edema, edema, localized edema, edema genital, eyelid edema, peripheral swelling, scrotal edema, and penile edema.
bMusculoskeletal pain includes arthralgia, back pain, bone pain, musculoskeletal chest pain, musculoskeletal pain, myalgia, neck pain, non-cardiac chest pain, pain in extremity, pain in jaw, spinal pain.
cFatigue includes fatigue and asthenia.
dPyrexia includes pyrexia and body temperature increased.
eCough includes cough, upper airway cough syndrome, and productive cough.
fPneumonia includes pneumonia aspiration, pneumonia, pneumonia influenzal, pneumonia bacterial, lower respiratory tract infection, and lung abscess.
gRash includes rash, dermatitis acneiform, rash maculo-papular, eczema, erythema multiforme, rash macular, dermatitis, rash erythematous, rash pustular, dermatitis bullous, and rash vesicular.
hDizziness includes dizziness, vertigo, and vertigo positional.

Clinically relevant adverse reactions occurring in < 10% of patients treated with TABRECTA included pruritus (including allergic pruritus), ILD/pneumonitis, cellulitis, acute kidney injury (including renal failure), urticaria, and acute pancreatitis.

Table 4 summarizes the laboratory abnormalities in GEOMETRY mono-1.

Table 4: Select Laboratory Abnormalities (≥ 20%) Worsening From Baseline in Patients Who Received TABRECTA in GEOMETRY mono-1
Laboratory abnormalities | TABRECTAa
 | Grades 1 to 4 (%) | Grades 3 to 4 (%)
Chemistry
Decreased albumin | 72 | 1.9
Increased creatinine | 65 | 0.5
Increased alanine aminotransferase | 39 | 9
Increased amylase | 34 | 4.7
Increased alkaline phosphatase | 32 | 0.6
Increased gamma-glutamyltransferase | 30 | 6
Increased lipase | 29 | 9
Increased aspartate aminotransferase | 28 | 6
Decreased phosphate | 26 | 4.4
Increased potassium | 25 | 4.1
Decreased sodium | 24 | 6
Decreased glucose | 23 | 0.3
Hematology
Decreased lymphocytes | 45 | 14
Decreased leukocytes | 25 | 1.7
Decreased hemoglobin | 24 | 2.8
aThe denominator used to calculate the rate varied from 359 to 364 based on the number of patients with a baseline value and at least one post-treatment value.

Other Clinical Trials Experience

The following adverse reactions have been reported following administration of TABRECTA: hypersensitivity and thrombocytopenia.

7 DRUG INTERACTIONS

7.1 Effect of Other Drugs on TABRECTA

Strong CYP3A Inhibitors

Coadministration of TABRECTA with a strong CYP3A inhibitor increased capmatinib exposure, which may increase the incidence and severity of adverse reactions of TABRECTA [see Clinical Pharmacology (12.3)]. Closely monitor patients for adverse reactions during coadministration of TABRECTA with strong CYP3A inhibitors.

Strong and Moderate CYP3A Inducers

Coadministration of TABRECTA with a strong CYP3A inducer decreased capmatinib exposure. Coadministration of TABRECTA with a moderate CYP3A inducer may also decrease capmatinib exposure. Decreases in capmatinib exposure may decrease TABRECTA anti-tumor activity [see Clinical Pharmacology (12.3)]. Avoid coadministration of TABRECTA with strong and moderate CYP3A inducers.

7.2 Effect of TABRECTA on Other Drugs

CYP1A2 Substrates

Coadministration of TABRECTA increased the exposure of a CYP1A2 substrate, which may increase the adverse reactions of these substrates [see Clinical Pharmacology (12.3)]. If coadministration is unavoidable between TABRECTA and CYP1A2 substrates where minimal concentration changes may lead to serious adverse reactions, decrease the CYP1A2 substrate dosage in accordance with the approved prescribing information.

P-glycoprotein (P-gp) and Breast Cancer Resistance Protein (BCRP) Substrates

Coadministration of TABRECTA increased the exposure of a P-gp substrate and a BCRP substrate, which may increase the adverse reactions of these substrates [see Clinical Pharmacology (12.3)]. If coadministration is unavoidable between TABRECTA and P-gp or BCRP substrates where minimal concentration changes may lead to serious adverse reactions, decrease the P-gp or BCRP substrate dosage in accordance with the approved prescribing information.

MATE1 and MATE2K Substrates

Coadministration of TABRECTA may increase the exposure of MATE1 and MATE2K substrates, which may increase the adverse reactions of these substrates [see Clinical Pharmacology (12.3)]. If coadministration is unavoidable between TABRECTA and MATE1 or MATE2K substrates where minimal concentration changes may lead to serious adverse reactions, decrease the MATE1 or MATE2K substrate dosage in accordance with the approved prescribing information.

8 USE IN SPECIFIC POPULATIONS

8.1 Pregnancy

Risk Summary

Based on findings from animal studies and its mechanism of action [see Clinical Pharmacology (12.1)], TABRECTA can cause fetal harm when administered to a pregnant woman. There are no available data on TABRECTA use in pregnant women. Oral administration of capmatinib to pregnant rats and rabbits during the period of organogenesis resulted in malformations at maternal exposures less than the human exposure based on AUC at the 400 mg twice daily clinical dose (see Data). Advise pregnant women of the potential risk to a fetus.

In the U.S. general population, the estimated background risk of major birth defects and miscarriage in clinically recognized pregnancies is 2% to 4% and 15% to 20%, respectively.

Data

Animal Data

In rats, maternal toxicity (reduced body weight gain and food consumption) occurred at 30 mg/kg/day (approximately 1.4 times the human exposure based on AUC at the 400 mg twice daily clinical dose). Fetal effects included reduced fetal weights, irregular/incomplete ossification, and increased incidences of fetal malformations (e.g., abnormal flexure/inward malrotation of hindpaws/forepaws, thinness of forelimbs, lack of/reduced flexion at the humerus/ulna joints, and narrowed or small tongue) at doses of ≥ 10 mg/kg/day (approximately 0.6 times the human exposure based on AUC at the 400 mg twice daily clinical dose).

In rabbits, no maternal effects were detected at doses up to 60 mg/kg/day (approximately 1.5 times the human exposure based on AUC at the 400 mg twice daily clinical dose). Fetal effects included small lung lobe at ≥ 5 mg/kg/day (approximately 0.016 times the human exposure based on AUC at the 400 mg twice daily clinical dose), and reduced fetal weights, irregular/incomplete ossification and increased incidences of fetal malformations (e.g., abnormal flexure/malrotation of hindpaws/forepaws, thinness of forelimbs/hindlimbs, lack of/reduced flexion at the humerus/ulna joints, small lung lobes, narrowed or small tongue) at the dose of 60 mg/kg/day.

8.2 Lactation

Risk Summary

There are no data on the presence of capmatinib or its metabolites in either human or animal milk or its effects on the breastfed child or on milk production. Because of the potential for serious adverse reactions in breastfed children, advise women not to breastfeed during treatment with TABRECTA and for 1 week after the last dose.

8.3 Females and Males of Reproductive Potential

Based on animal data, TABRECTA can cause malformations at doses less than the human exposure based on AUC at the 400 mg twice daily clinical dose [see Use in Specific Populations (8.1)].

Pregnancy Testing

Verify pregnancy status for females of reproductive potential prior to starting treatment with TABRECTA.

Contraception

Females

Advise females of reproductive potential to use effective contraception during treatment with TABRECTA and for 1 week after the last dose.

Males

Advise males with female partners of reproductive potential to use effective contraception during treatment with TABRECTA and for 1 week after the last dose.

8.4 Pediatric Use

Safety and effectiveness of TABRECTA in pediatric patients have not been established.

8.5 Geriatric Use

In GEOMETRY mono-1, 61% of the 373 patients were 65 years or older and 18% were 75 years or older. No overall differences in the safety or effectiveness were observed between these patients and younger patients.

8.6 Renal Impairment

No dosage adjustment is recommended in patients with mild (baseline creatinine clearance [CLcr] 60 to 89 mL/min by Cockcroft-Gault) or moderate renal impairment (CLcr 30 to 59 mL/min) [see Clinical Pharmacology (12.3)]. TABRECTA has not been studied in patients with severe renal impairment (CLcr 15 to 29 mL/min).

11 DESCRIPTION

Capmatinib is a kinase inhibitor. The chemical name is 2-Fluoro-N-methyl-4-[7-(quinolin-6-ylmethyl)imidazo[1,2-b][1,2,4]triazin-2-yl]benzamide—hydrogen chloride—water (1/2/1). The molecular formula for capmatinib dihydrochloride monohydrate is C23H21Cl2FN6O2. The relative molecular mass is 503.36 g/mol for the dihydrochloride monohydrate salt and 412.43 g/mol for the free base. The chemical structure for capmatinib dihydrochloride monohydrate is shown below:

Capmatinib dihydrochloride monohydrate is a yellow powder with a pKa1 of 0.9 (calculated) and pKa2 of 4.5 (experimentally). Capmatinib dihydrochloride monohydrate is slightly soluble in acidic aqueous solutions at pH 1 and 2 and of further decreasing solubility towards neutral condition. The log of the distribution coefficient (n-octanol/acetate buffer pH 4.0) is 1.2.

TABRECTA is supplied for oral use as ovaloid, curved film-coated tablets with beveled edges, unscored containing 150 mg (pale orange brown color) or 200 mg (yellow color) capmatinib (equivalent to 183.00 mg or 244.00 mg respectively of capmatinib dihydrochloride monohydrate). Each tablet strength contains colloidal silicon dioxide; crospovidone; magnesium stearate; mannitol; microcrystalline cellulose; povidone; and sodium lauryl sulfate as inactive ingredients.

The 150 mg tablet coating contains ferric oxide, red; ferric oxide, yellow; ferrosoferric oxide; hypromellose; polyethylene glycol (PEG) 4000; talc; and titanium dioxide. The 200 mg tablet coating contains ferric oxide, yellow; hypromellose; polyethylene glycol (PEG) 4000; talc; and titanium dioxide.

12 CLINICAL PHARMACOLOGY

12.1 Mechanism of Action

Capmatinib is a kinase inhibitor that targets MET, including the mutant variant produced by exon 14 skipping. MET exon 14 skipping results in a protein with a missing regulatory domain that reduces its negative regulation leading to increased downstream MET signaling. Capmatinib inhibited cancer cell growth driven by a mutant MET variant lacking exon 14 at clinically achievable concentrations and demonstrated anti-tumor activity in murine tumor xenograft models derived from human lung tumors with either a mutation leading to MET exon 14 skipping or MET amplification. Capmatinib inhibited the phosphorylation of MET triggered by binding of hepatocyte growth factor or by MET amplification, as well as MET-mediated phosphorylation of downstream signaling proteins and proliferation and survival of MET-dependent cancer cells.

12.2 Pharmacodynamics

Exposure-Response

Capmatinib exposure-response relationships and the time course of pharmacodynamics response are unknown.

Cardiac Electrophysiology

No large mean increase in QTc (i.e. > 20 ms) was detected following treatment with TABRECTA at the recommended dosage of 400 mg orally twice daily.

12.3 Pharmacokinetics

Capmatinib exposure (AUC0-12h and Cmax) increased approximately proportionally over a dose range of 200 mg (0.5 times the recommended dosage) to 400 mg. Capmatinib reached steady-state by day 3 following twice daily dosing, with a mean (% coefficient of variation [%CV]) accumulation ratio of 1.5 (41%).

Absorption

After administration of TABRECTA 400 mg orally in patients with cancer, capmatinib peak plasma concentrations (Cmax) were reached in approximately 1 to 2 hours (Tmax). The absorption of capmatinib after oral administration is estimated to be greater than 70%.

Effect of Food

A high-fat meal (containing approximately 1000 calories and 50% fat) in healthy subjects increased capmatinib AUC0-INF by 46% with no change in Cmax compared to under fasted conditions. A low-fat meal (containing approximately 300 calories and 20% fat) in healthy subjects had no clinically meaningful effect on capmatinib exposure. When capmatinib was administered at 400 mg orally twice daily in cancer patients, exposure (AUC0-12h) was similar after administration of capmatinib with food and under fasted conditions.

Distribution

Capmatinib plasma protein binding is 96%, independent of capmatinib concentration. The apparent mean volume of distribution at steady-state is 164 L.

The blood-to-plasma ratio was 1.5, but decreased at higher concentrations to 0.9.

Elimination

The effective elimination half-life of capmatinib is 6.5 hours. The mean (%CV) steady-state apparent clearance of capmatinib is 24 L/hr (82%).

Metabolism

Capmatinib is primarily metabolized by CYP3A4 and aldehyde oxidase.

Excretion

Following a single oral administration of radiolabeled-capmatinib to healthy subjects, 78% of the total radioactivity was recovered in feces with 42% as unchanged and 22% was recovered in urine with negligible as unchanged.

Specific Populations

No clinically significant effects on the pharmacokinetic parameters of capmatinib were identified for the following covariates assessed: age (26 to 90 years), sex, race (White, Asian, Native American, Black, unknown), body weight (35 to 131 kg), mild to moderate renal impairment (baseline CLcr 30 to 89 mL/min by Cockcroft-Gault) and mild, moderate or severe hepatic impairment (Child-Pugh classification). The effect of severe renal impairment (baseline CLcr 15 to 29 mL/min) on capmatinib pharmacokinetics has not been studied.

Drug Interaction Studies

Clinical Studies and Model-Informed Approaches

Strong CYP3A Inhibitors: Coadministration with itraconazole (a strong CYP3A inhibitor) increased capmatinib AUC0-INF by 42% with no change in capmatinib Cmax.

Strong CYP3A Inducers: Coadministration with rifampicin (a strong CYP3A inducer) decreased capmatinib AUC0-INF by 67% and decreased Cmax by 56%.

Moderate CYP3A Inducers: Coadministration with efavirenz (a moderate CYP3A inducer) was predicted to decrease capmatinib AUC0-12h by 44% and decrease Cmax by 34%.

Proton Pump Inhibitors: Coadministration with rabeprazole (a proton pump inhibitor) decreased capmatinib AUC0-INF by 25% and decreased Cmax by 38%.

Substrates of CYP Enzymes: Coadministration of capmatinib increased caffeine (a CYP1A2 substrate) AUC0-INF by 134% with no change in its Cmax. Coadministration of capmatinib had no clinically meaningful effect on exposure of midazolam (a CYP3A substrate).

P-gp Substrates: Coadministration of capmatinib increased digoxin (a P-gp substrate) AUC0-INF by 47% and increased Cmax by 74%.

BCRP Substrates: Coadministration of capmatinib increased rosuvastatin (a BCRP substrate) AUC0-INF by 108% and increased Cmax by 204%.

In Vitro Studies

Transporter Systems: Capmatinib is a substrate of P-gp, but not a substrate of BCRP or MRP2. Capmatinib reversibly inhibits MATE1 and MATE2K, but does not inhibit OATP1B1, OATP1B3, OCT1, OAT1, OAT3, or MRP2.

13 NONCLINICAL TOXICOLOGY

13.1 Carcinogenesis, Mutagenesis, Impairment of Fertility

Carcinogenicity studies were not conducted with capmatinib. Capmatinib was not mutagenic in an in vitro bacterial reverse mutation assay and did not cause chromosomal aberrations in an in vitro chromosome aberration assay in human peripheral blood lymphocytes. Capmatinib was not clastogenic in an in vivo bone marrow micronucleus test in rats.

Dedicated fertility studies were not conducted with capmatinib. No effects on male and female reproductive organs occurred in general toxicology studies conducted in rats and monkeys at doses resulting in exposures of up to approximately 3.6 times the human exposure based on AUC at the 400 mg twice daily clinical dose.

13.2 Animal Toxicology and/or Pharmacology

In rats, capmatinib administration resulted in vacuolation of white matter of the brain in both 4- and 13-week studies at doses ≥ 2.2 times the human exposure (AUC) at the 400 mg twice daily clinical dose. In some cases, the brain lesions were associated with early death and/or convulsions or tremors. Concentrations of capmatinib in the brain tissue of rats was approximately 9% of the corresponding concentrations in plasma.

In vitro and in vivo assays demonstrated that capmatinib has some potential for photosensitization; however, the no-observed-adverse-effect level for in vivo photosensitization was 30 mg/kg/day (Cmax of 14000 ng/mL), about 2.9 times the human Cmax at the 400 mg twice daily clinical dose.

14 CLINICAL STUDIES

Metastatic NSCLC with a Mutation that Leads to MET Exon 14 Skipping

The efficacy of TABRECTA was evaluated in GEOMETRY mono-1, a multicenter, non-randomized, open-label, multi-cohort study (NCT02414139). Eligible patients were required to have NSCLC with a mutation that leads to MET exon 14 skipping, epidermal growth factor receptor (EGFR) wild-type and anaplastic lymphoma kinase (ALK) negative status, and at least one measurable lesion as defined by Response Evaluation Criteria in Solid Tumors (RECIST) version 1.1. Patients with symptomatic CNS metastases, clinically significant uncontrolled cardiac disease, or who received treatment with any MET or hepatocyte growth factor (HGF) inhibitor were not eligible for the study.

Out of the first 97 patients enrolled in GEOMETRY mono-1 following the central confirmation of MET exon 14 skipping by a RNA-based clinical trial assay, 78 patient samples were retested with the FDA-approved FoundationOne® CDx (22 treatment-naïve and 56 previously treated patients) to detect mutations that lead to MET exon 14 skipping. Out of 78 samples retested with FoundationOne® CDx, 73 samples were evaluable (20 treatment-naïve and 53 previously treated patients), 72 (20 treatment-naïve and 52 previously treated patients) of which were confirmed to have a mutation that leads to MET exon 14 skipping, demonstrating an estimated positive percentage agreement of 99% (72/73) between the clinical trial assay and the FDA-approved assay.

Patients received TABRECTA 400 mg orally twice daily until disease progression or unacceptable toxicity. The major efficacy outcome measure was overall response rate (ORR) as determined by a Blinded Independent Review Committee (BIRC) according to RECIST 1.1. An additional efficacy outcome measure was duration of response (DOR) by BIRC.

The efficacy population included 60 treatment-naïve patients and 100 previously treated patients. The median age was 71 years (range: 48 to 90 years); 61% female; 77% White; 25% had Eastern Cooperative Oncology Group (ECOG) Performance Status (PS) 0 and 74% had ECOG PS 1; 61% never smoked; 83% had adenocarcinoma; and 16% had CNS metastases. Among previously treated patients, 81% received one, 16% received two and 3% received three prior lines of systemic therapy. Amongst previously treated patients, 86% received prior platinum-based chemotherapy.

Efficacy results are presented in Table 5.

Table 5: Efficacy Results for Treatment-Naïve and Previously Treated Patients in GEOMETRY mono-1
Efficacy parameters | Treatment-naïve N = 60 | Previously treated N = 100
Overall response ratea,b (95% CI)c | 68% (55, 80) | 44% (34, 54)
Complete response | 5% | 0
Partial response | 63% | 44%
Duration of response (DOR)a
Median (months) (95% CI)d | 16.6 (8.4, 22.1) | 9.7 (5.6, 13.0)
Patients % with DOR ≥ 12 months | 49% | 36%
Abbreviations: CI, confidence interval; NE, not estimable.
aBlinded Independent Review Committee (BIRC) review.
bConfirmed response.
cClopper and Pearson exact binomial 95% CI.
dBased on Kaplan-Meier estimate.

16 HOW SUPPLIED/STORAGE AND HANDLING

How Supplied

TABRECTA (capmatinib) 150 mg and 200 mg tablets
Strength | Description | Tablets per bottle | NDC number
150 mg | Pale orange brown, ovaloid, curved film-coated tablet with beveled edges, unscored, debossed with ‘DU’ on one side and ‘NVR’ on the other side. | 56 | 0078-0709-56
200 mg | Yellow, ovaloid, curved film-coated tablet with beveled edges, unscored, debossed with ‘LO’ on one side and ‘NVR’ on the other side. | 56 | 0078-0716-56

Storage

Dispense in the original package with the desiccant cartridge. Store at 20°C to 25°C (68°F to 77°F), excursions permitted between 15°C and 30°C (59°F and 86°F) [see USP Controlled Room Temperature]. Protect from moisture.

Discard any unused TABRECTA remaining after 6 weeks of first opening the bottle.

17 PATIENT COUNSELING INFORMATION

Advise the patient to read the FDA-approved patient labeling (Patient Information).

Interstitial Lung Disease (ILD)/Pneumonitis

Inform patients of the risks of severe or fatal ILD/pneumonitis. Advise patients to immediately contact their healthcare provider for new or worsening respiratory symptoms [see Warnings and Precautions (5.1)].

Hepatotoxicity

Inform patients that they will need to undergo lab tests to monitor liver function. Advise patients to immediately contact their healthcare provider for signs and symptoms of liver dysfunction [see Warnings and Precautions (5.2)].

Pancreatic Toxicity

Inform patients that they will need to undergo lab tests to monitor pancreatic function. Advise patients to immediately contact their healthcare provider for signs and symptoms of pancreatitis [see Warnings and Precautions (5.3)].

Hypersensitivity Reactions

Inform patients that there is a risk of hypersensitivity reactions with TABRECTA. Advise patients to stop taking TABRECTA and immediately contact their healthcare provider for signs and symptoms of hypersensitivity [see Warnings and Precautions (5.4)].

Risk of Photosensitivity

Inform patients that there is a potential risk of photosensitivity reactions with TABRECTA. Advise patients to limit direct ultraviolet exposure by using sunscreen or protective clothing during treatment with TABRECTA [see Warnings and Precautions (5.5)].

Embryo-Fetal Toxicity

Advise pregnant women of the potential risk to a fetus. Advise females of reproductive potential to inform their healthcare provider of a known or suspected pregnancy [see Warnings and Precautions (5.6), Use in Specific Populations (8.1)].

Advise females of reproductive potential to use effective contraception during treatment with TABRECTA and for 1 week after the last dose [see Use in Specific Populations (8.3)].

Advise males with female partners of reproductive potential to use effective contraception during treatment with TABRECTA and for 1 week after the last dose [see Use in Specific Populations (8.3)].

Drug Interactions

Advise patients to inform their healthcare providers of all concomitant medications, including prescription medicines, over-the-counter drugs, vitamins, and herbal products [see Drug Interactions (7)].

Lactation

Advise women not to breastfeed during treatment with TABRECTA and for 1 week after the last dose [see Use in Specific Populations (8.2)].

Distributed by:
Novartis Pharmaceuticals Corporation
East Hanover, New Jersey 07936

© Novartis

T2024-19

PATIENT INFORMATION
TABRECTA® (ta brek tah)
(capmatinib) tablets

What is TABRECTA?
TABRECTA is a prescription medicine used to treat adults with a kind of lung cancer called non-small cell lung cancer (NSCLC) that:

- has spread to other parts of the body (metastatic), and
- whose tumors have an abnormal mesenchymal epithelial transition (MET) gene. Your healthcare provider will perform a test to make sure that TABRECTA is right for you.

It is not known if TABRECTA is safe and effective in children.

Before taking TABRECTA, tell your healthcare provider about all of your medical conditions, including if you:

- have or have had lung or breathing problems other than your lung cancer
- have or have had liver problems
- have or have had pancreatic problems
- are pregnant or plan to become pregnant. TABRECTA can harm your unborn baby.
  Females who are able to become pregnant:
  - Your healthcare provider should do a pregnancy test before you start your treatment with TABRECTA.
  - You should use effective birth control during treatment and for 1 week after your last dose of TABRECTA. Talk to your healthcare provider about birth control choices that might be right for you during this time.
  - Tell your healthcare provider right away if you become pregnant or think you may be pregnant during treatment with TABRECTA.
  Males who have female partners who can become pregnant:
  - You should use effective birth control during treatment and for 1 week after your last dose of TABRECTA.
- are breastfeeding or plan to breastfeed. It is not known if TABRECTA passes into your breast milk. Do not breastfeed during treatment and for 1 week after your last dose of TABRECTA.

Tell your healthcare provider about all the medicines you take, including prescription and over-the-counter medicines, vitamins, and herbal supplements.

How should I take TABRECTA?

- Take TABRECTA exactly as your healthcare provider tells you.
- Take TABRECTA 2 times a day with or without food.
- Swallow TABRECTA tablets whole. Do not break, crush, or chew TABRECTA tablets.
- Do not change your dose or stop taking TABRECTA unless your healthcare provider tells you to.
- If you miss or vomit a dose of TABRECTA, do not make up the dose. Take your next dose at your regular scheduled time.

What should I avoid while taking TABRECTA?

- Your skin may be sensitive to the sun (photosensitivity) during treatment with TABRECTA. Use sunscreen or wear clothes that cover your skin during your treatment with TABRECTA to limit direct sunlight exposure.

What are the possible side effects of TABRECTA?
TABRECTA may cause serious side effects, including:

- Lung or breathing problems. TABRECTA may cause inflammation of the lungs that can cause death. Tell your healthcare provider right away if you develop any new or worsening symptoms, including:

◦ cough

◦ fever

◦ trouble breathing or shortness of breath

- Liver problems. TABRECTA may cause abnormal liver blood test results. Your healthcare provider will do blood tests to check your liver function before you start treatment and during treatment with TABRECTA. Tell your healthcare provider right away if you develop any signs and symptoms of liver problems, including:

◦ your skin or the white part of your eyes turns yellow (jaundice)
◦ dark or “tea-colored” urine
◦ light-colored stools (bowel movements)
◦ confusion
◦ tiredness
◦ loss of appetite for several days or longer

◦ nausea and vomiting
◦ pain, aching, or tenderness on the right side of your stomach-area (abdomen)
◦ weakness
◦ swelling in your stomach-area

- Pancreas problems. TABRECTA may cause increases in your blood amylase and/or lipase levels that may indicate a problem with your pancreas. Your healthcare provider will do blood tests to check your pancreatic function before you start treatment and during treatment with TABRECTA. Tell your healthcare provider right away if you develop any signs and symptoms of pancreas problems, including:
  - upper stomach (abdominal) pain that may spread to your back and get worse with eating
  - weight loss
  - nausea
  - vomiting

- Allergic reactions. TABRECTA can cause an allergic reaction. Stop taking TABRECTA and tell your healthcare provider right away if you get any signs and symptoms of an allergic reaction, including:

◦ fever
◦ chills
◦ itching
◦ rash

◦ dizziness or feeling faint
◦ nausea
◦ vomiting

- Risk of sensitivity to sunlight (photosensitivity). See “What should I avoid while taking TABRECTA?”

The most common side effects of TABRECTA include:

• swelling of your hands or feet
• nausea
• muscle or bone pain
• tiredness and weakness
• vomiting

• trouble breathing
• cough
• loss of appetite
• changes in certain blood tests

Your healthcare provider may change your dose, temporarily stop, or permanently stop treatment with TABRECTA if you develop certain side effects.
These are not all of the possible side effects of TABRECTA.
Call your doctor for medical advice about side effects. You may report side effects to FDA at 1-800-FDA-1088.

How should I store TABRECTA?

- Store TABRECTA at room temperature between 68°F to 77°F (20°C to 25°C).
- Store TABRECTA in the original package with the drying agent (desiccant) cartridge.
- Protect TABRECTA from moisture.
- Throw away (discard) any unused TABRECTA you have left after 6 weeks of first opening the bottle.

Keep TABRECTA and all medicines out of the reach of children.

General information about the safe and effective use of TABRECTA.
Medicines are sometimes prescribed for purposes other than those listed in a Patient Information leaflet. Do not use TABRECTA for a condition for which it was not prescribed. Do not give TABRECTA to other people, even if they have the same symptoms you have. It may harm them. You can ask your pharmacist or healthcare provider for information about TABRECTA that is written for health professionals.

What are the ingredients in TABRECTA?
Active ingredient: capmatinib
Inactive ingredients: Tablet core: colloidal silicon dioxide; crospovidone; magnesium stearate; mannitol; microcrystalline cellulose; povidone; and sodium lauryl sulfate.
Tablet coating (150 mg): ferric oxide, red; ferric oxide, yellow; ferrosoferric oxide; hypromellose; polyethylene glycol (PEG) 4000; talc; and titanium dioxide.
Tablet coating (200 mg): ferric oxide, yellow; hypromellose; polyethylene glycol (PEG) 4000; talc; and titanium dioxide.
Distributed by: Novartis Pharmaceuticals Corporation, East Hanover, New Jersey 07936
For more information, go to www.TABRECTA.com or call 1-888-669-6682.
© Novartis

This Patient Information has been approved by the U.S. Food and Drug Administration.

Revised: March 2025

T2025-11

PRINCIPAL DISPLAY PANEL

NDC 0078-0709-56

TABRECTA®

(capmatinib) tablets

150 mg*

Attention: Dispense and store Tabrecta
in original container with the desiccant
to protect from moisture.

Rx only

56 Film-coated tablets

NOVARTIS

PRINCIPAL DISPLAY PANEL

NDC 0078-0716-56

TABRECTA®

(capmatinib) tablets

200 mg*

Attention: Dispense and store Tabrecta
in original container with the desiccant
to protect from moisture.

Rx only

56 Film-coated tablets

NOVARTIS